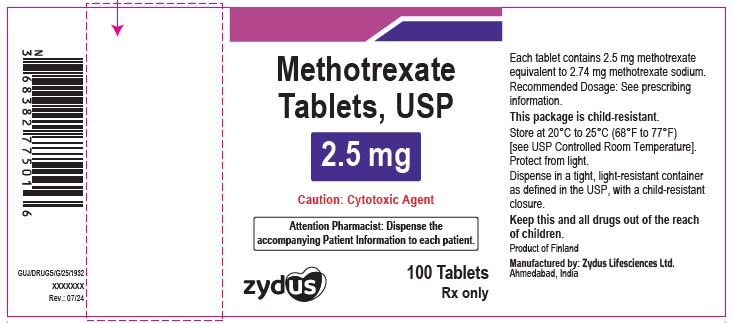 DRUG LABEL: Methotrexate
NDC: 70771-1058 | Form: TABLET
Manufacturer: Zydus Lifesciences Limited
Category: prescription | Type: HUMAN PRESCRIPTION DRUG LABEL
Date: 20241205

ACTIVE INGREDIENTS: METHOTREXATE 2.5 mg/1 1
INACTIVE INGREDIENTS: ANHYDROUS LACTOSE; CELLULOSE, MICROCRYSTALLINE; LACTOSE MONOHYDRATE; MAGNESIUM STEARATE; STARCH, CORN

Methotrexate tablet, USP

PACKAGE LABEL.PRINCIPAL DISPLAY PANEL

NDC 70771-1058-1

Methotrexate tablets, USP 2.5 mg

Rx only

36 tablets